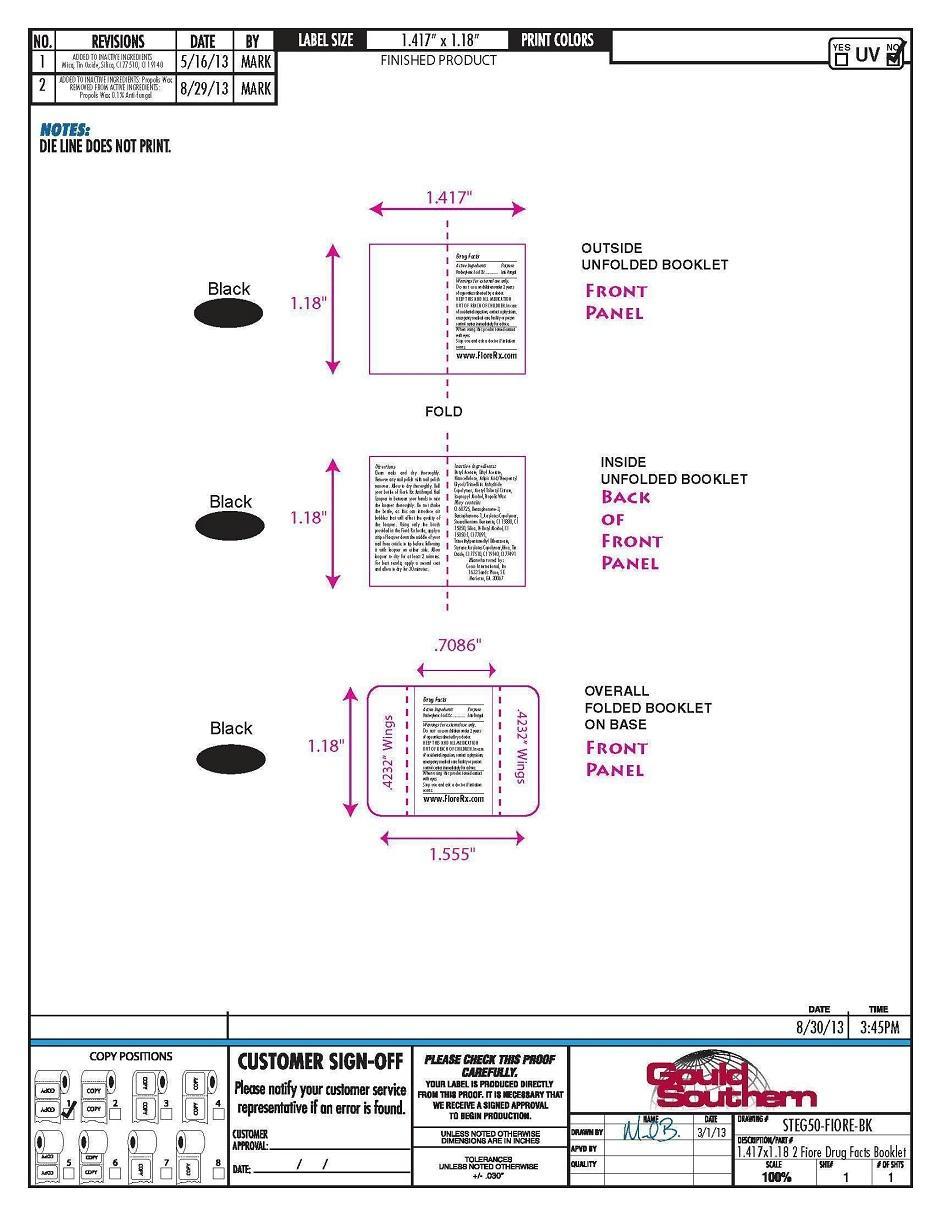 DRUG LABEL: Fiore Rx Pixie Dust Pink Antifungal Nail Polish
NDC: 52261-0204 | Form: FILM
Manufacturer: Cosco International, Inc.
Category: otc | Type: HUMAN OTC DRUG LABEL
Date: 20130919

ACTIVE INGREDIENTS: Undecylenic Acid 0.45 g/15 mL
INACTIVE INGREDIENTS: Butyl Acetate 6.2260095 g/15 mL; Ethyl Acetate 2.527011 g/15 mL; Pyroxylin 1.979754 g/15 mL; POLYESTER-10 1.41411015 g/15 mL; Acetyltributyl Citrate 0.98987715 g/15 mL; Isopropyl Alcohol 0.84846615 mL/15 mL; DIMETHYLAMINOETHYL METHACRYLATE - BUTYL METHACRYLATE - METHYL METHACRYLATE COPOLYMER 0.141411 g/15 mL; Bentoquatam 0.1272684 g/15 mL; TITANIUM DIOXIDE 0.0973554 g/15 mL; BUTYL ALCOHOL 0.07071285 g/15 mL; Silicon Dioxide 0.04242765 g/15 mL; Benzoresorcinol 0.02828505 g/15 mL; MICA 0.0267153 g/15 mL; PROPOLIS WAX 0.015 g/15 mL; Trimethylpentanediyl Dibenzoate 0.0141426 g/15 mL; D&C RED NO. 34 0.0007122 g/15 mL; D&C RED NO. 6 0.00037785 g/15 mL; STANNIC OXIDE 0.00036345 g/15 mL

Drug Facts

Active Ingredient Purpose
Undecylenic Acid 3%........................Anti-fungal

PURPOSE

Anti-fungal

Warnings For external use only.

Do not use on children under 2 years of age unless directed by a doctor.

KEEP THIS AND ALL MEDICATION OUT OF REACH OF CHILDREN.

In case of accidental ingestion, contact a physician, emergency medical care facility or poison control center immediately for advice.

When using this product avoid contact with eyes.

Stop use and ask a doctor if irritation occurs.

Directions

Clean nails and dry thoroughly.

Remove any nail polish with nail

polish remover. Allow to dry

thoroughly. Roll your bottle of Fioré

Rx Antifungal Nail Lacquer in between

your hands to mix the lacquer

thoroughly. Do not shake the bottle,

as this can introduce air bubbles that

will affect the quality of the lacquer.

Using only the brush provided in the

Fioré Rx bottle, apply a strip of

lacquer down the middle of your nail

from cuticle to tip before following it

with lacquer on either side. Allow

lacquer to dry for at least 2 minutes.

For best results, apply a second coat

and allow to dry for 30 minutes.

Inactive ingredients

Butyl acetate, ethyl acetate, nitrocellulose, adipic acid/neopentyl glycol/trimellitic copolymer, acetyl tributyl citrate, isopropyl alcohol, propolis wax

May contain:

CI 60725, Benzophenone-3,

Bensophenone-1, Acrylates Copolymer,

Stearalkonium Bentonite, CI 15880, CI

15850, Silica, N-Butyl Alcohol, CI

15850:1, CI 77891,

Trimethylpentanediyl Dibenzoate,

Styrene Acrylates Copolymer,Mica, Tin

Oxide, CI 77510, CI 19140, CI 77491